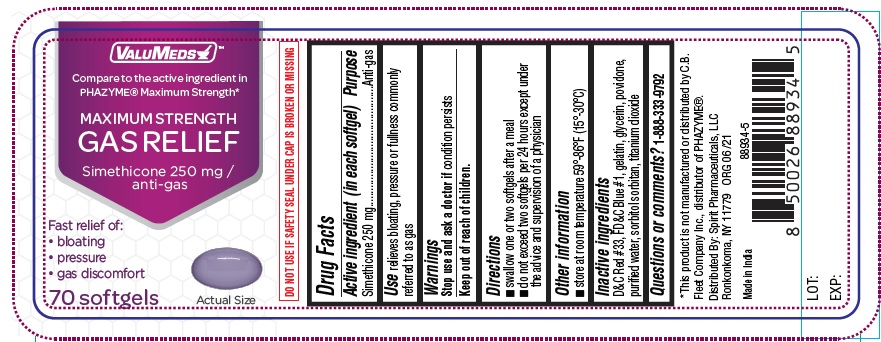 DRUG LABEL: Maximum Strength Gas Relief
NDC: 68210-4165 | Form: CAPSULE, GELATIN COATED
Manufacturer: Spirit Pharmaceuticals LLC
Category: otc | Type: HUMAN OTC DRUG LABEL
Date: 20241213

ACTIVE INGREDIENTS: DIMETHICONE 250 mg/1 1
INACTIVE INGREDIENTS: FD&C BLUE NO. 1; GELATIN; GLYCERIN; POVIDONE; SORBITOL SOLUTION; WATER; D&C RED NO. 33

Maximum Strength Gas Relief

Active ingredient (in each softgel)

Simethicone 250 mg

Purpose

Anti-gas

Use

- relieves bloating, pressure or fullness commonly referred to as gas

Warnings

Stop use and ask a doctor if

condition persists

Keep out of reach of children.

Directions

- swallow one or two softgels after a meal
- do not exceed two softgels per 24 hours except under the advice and supervision of a physician

Other information

- store at room temperature 59°-86°F (15°-30°C)

Inactive ingredients

D&C Red #33, FD&C Blue #1, gelatin, glycerin, povidone, purified water, sorbitol sorbitan, titanium dioxide

Questions or Comments?

1-888-333-9792

PRINCIPAL DISPLAY PANEL

VALUMEDS MAXIMUM STRENGTH GAS RELIEF

SIMETHICONE 250 mg/ Anti-gas

Compare to the active ingredient in PHAZYME® Maximum Strength*

*This product is not manufactured or distributed by C.B.
Fleet Company Inc., distributor of PHAZYME®.

70 SOFTGELS